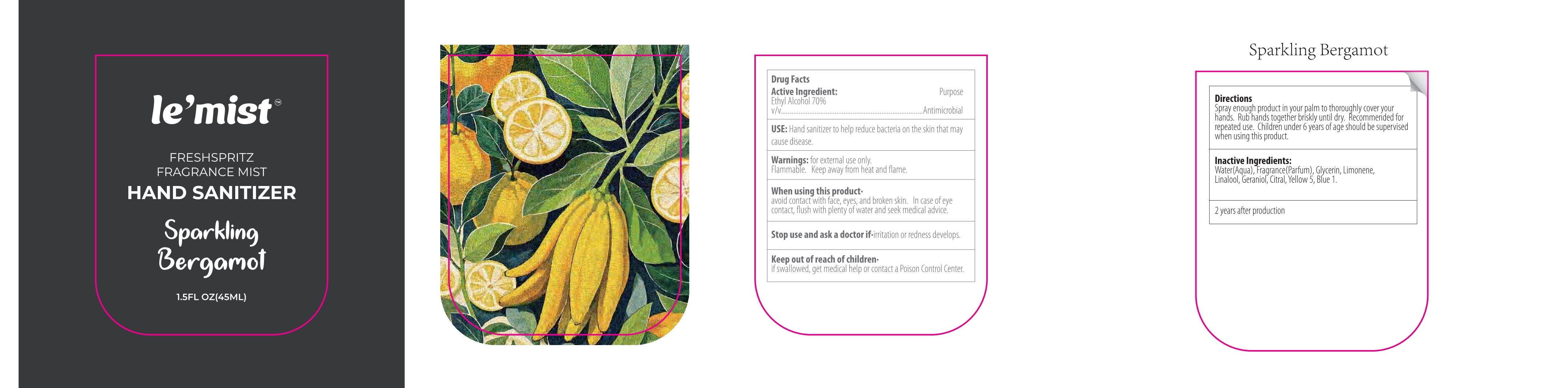 DRUG LABEL: Sparkling Bergamot Hand Sanitizer
NDC: 41366-082 | Form: LIQUID
Manufacturer: Zhejiang Meimi Technology Co., Ltd.
Category: otc | Type: HUMAN OTC DRUG LABEL
Date: 20250610

ACTIVE INGREDIENTS: ALCOHOL 70 mL/100 mL
INACTIVE INGREDIENTS: BLUE 1; GLYCERIN; WATER; LIMONENE, (+)-; LINALOOL; YELLOW 5; GERANIOL; CITRAL

Zhejiang Meimi Technology Co., Ltd.
Sparkling Bergamot Hand Sanitizer 45ml
41366-082-01

Active Ingredient(s)

Ethyl Alcohol 70% v/v

Purpose

Antimicrobial

Use

Hand sanitizer to help reduce bacteria on the skin that may cause disease.

Warnings

- for external use only.
- Flammable.
- Keep away from heat and flame.

Stop use and ask a doctor if·irritation or redness develops.

Keep out of reach of children·
if swallowed, get medical help or contact a Poison Control Center.

Directions

Spray enough product in your palm to thoroughly cover your hands. Rub hands together briskly until dry. Recommended for repeated use. Children under 6 years of age should be supervised when using this product.

Inactive ingredients

Water(Aqua), Fragrance(Parfum), Glycerin, Limonene, Linalool, Geraniol, Citral, Yellow 5, Blue 1.

When using this product·
avoid contact with face, eyes, and broken skin. In case of eye contact, flush with plenty of water and seek medical advice.

Package Label - Principal Display Panel

45ml in 1 bottle

41366-082-01